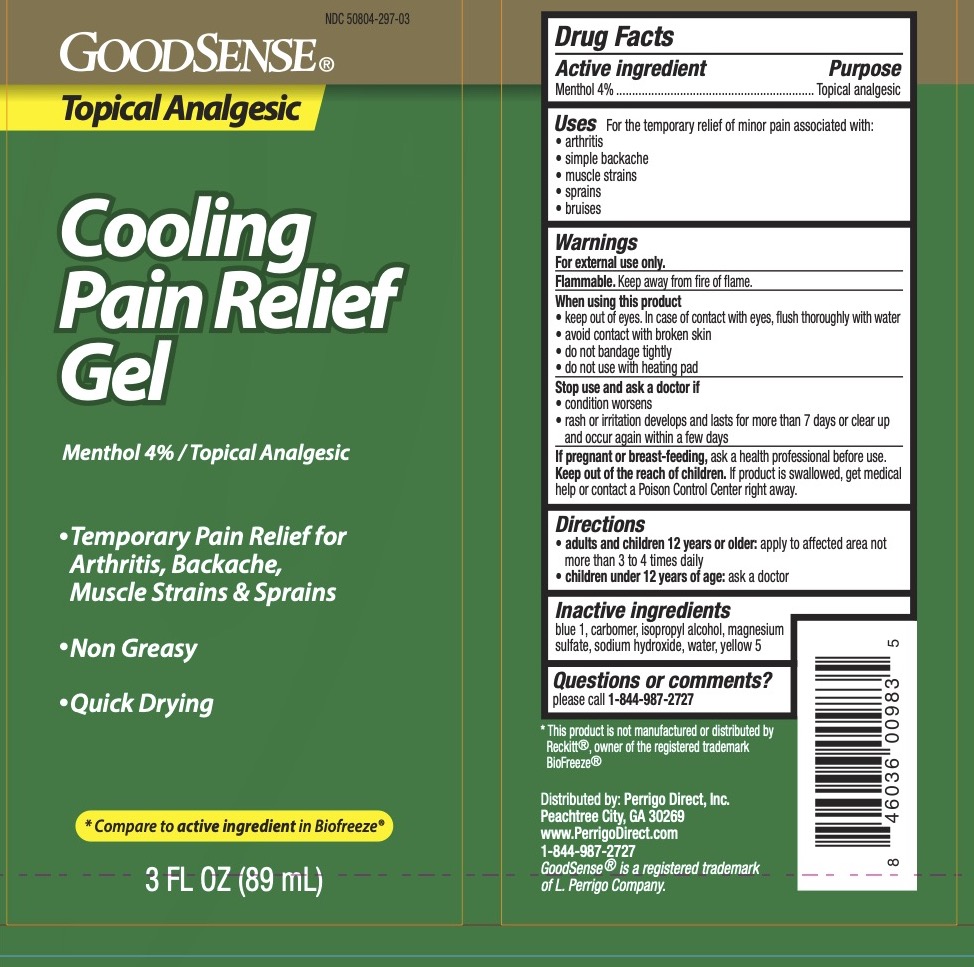 DRUG LABEL: GoodSense Cooling Pain Relief
NDC: 50804-297 | Form: GEL
Manufacturer: Geiss, Destin & Dunn, Inc
Category: otc | Type: HUMAN OTC DRUG LABEL
Date: 20250720

ACTIVE INGREDIENTS: MENTHOL 4 g/100 mL
INACTIVE INGREDIENTS: WATER; ISOPROPYL ALCOHOL; CARBOMER 940; MAGNESIUM SULFATE; FD&C BLUE NO. 1; FD&C YELLOW NO. 5; SODIUM HYDROXIDE

GoodSense Cooling Pain Relief Gel

ACTIVE INGREDIENT

Menthol 4%

PURPOSE

Topical Analgesic.

DOSAGE AND ADMINISTRATION

For the temporary relief of minor pain associated with arthritis, simple backache, muscle strains, sprains, and bruises.

WARNINGS

For external use only.

When using this product keep out of eyes. In case of contact with eyes, flush thoroughly with water, avoid contact with broken skin, do not bandage tightly, and do not use with heating pad.

Stop use and ask a doctor if the condition worsens, rash or irritation develops and lasts for more than 7 days or clear up and occur again within a few days.

PREGNANCY OR BREAST FEEDING

Ask a health professional before use.

Keep out of reach of children. If the product is swallowed, get medical help or contact a Poison Control Center right away.

INDICATIONS AND USAGE

Adults and children 12 years and older: apply to the affected area, not more than 3 to 4 times a day. Children under 12 years of age: ask a doctor.

INACTIVE INGREDIENT

Blue 1, carbomer, isopropyl alcohol, magnesium sulfate, sodium hydroxide, water, and yellow 5.